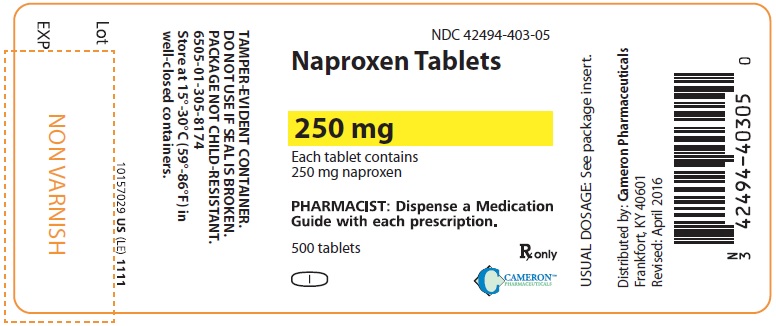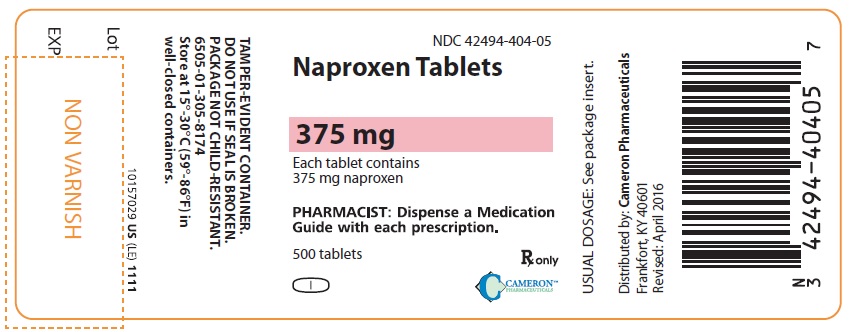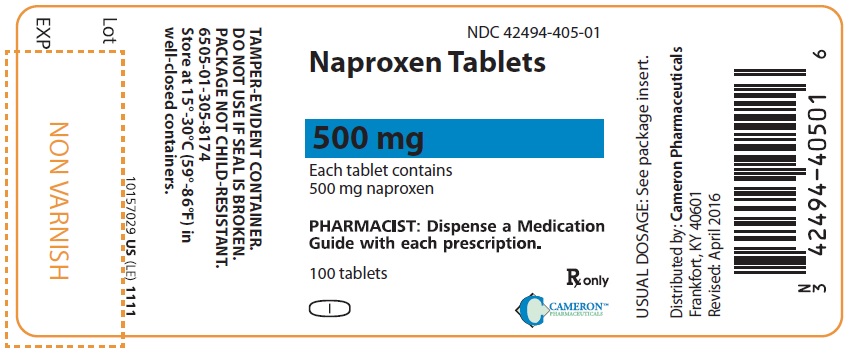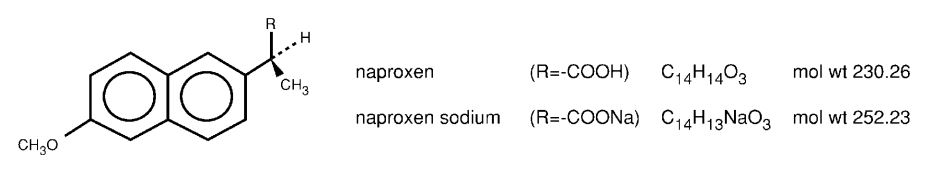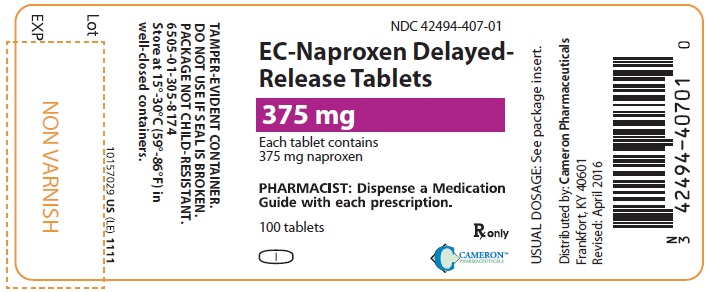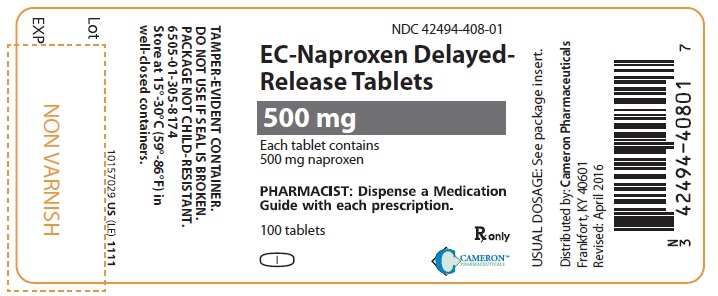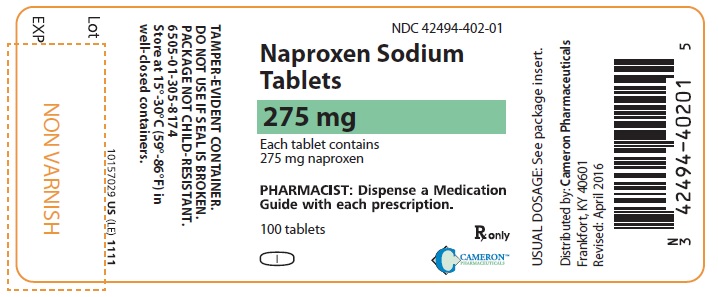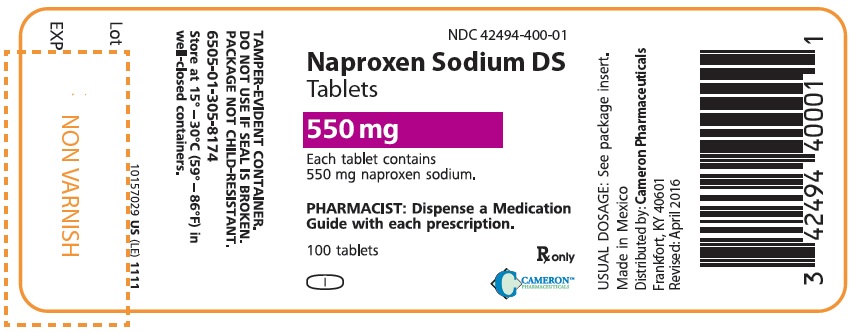 DRUG LABEL: NAPROXEN
NDC: 42494-403 | Form: TABLET
Manufacturer: Cameron Pharmaceuticals, LLC
Category: prescription | Type: HUMAN PRESCRIPTION DRUG LABEL
Date: 20160811

ACTIVE INGREDIENTS: naproxen 250 mg/1 1
INACTIVE INGREDIENTS: croscarmellose sodium; ferric oxide red; povidone K90; magnesium stearate

Naproxen

Rx only

WARNING: RISK OF SERIOUS CARDIOVASCULAR AND GASTROINTESTINAL EVENTS

Cardiovascular Thrombotic Events

• Nonsteroidal anti-inflammatory drugs (NSAIDs) may cause an increased risk of serious cardiovascular thrombotic events, myocardial infarction, and stroke, which can be fatal. This risk may increase with duration of use (see WARNINGS).

• NAPROXEN, EC-NAPROXEN, NAPROXEN SODIUM and/ NAPROXEN SODIUM DS are contraindicated for the treatment of peri-operative pain in the setting of coronary artery bypass graft (CABG) surgery (see CONTRAINDICATIONS, WARNINGS).

Gastrointestinal Bleeding, Ulceration, and Perforation

• NSAIDs cause an increased risk of serious gastrointestinal (GI) adverse events including bleeding, ulceration, and perforation of the stomach or intestines, which can be fatal. These events can occur at any time during use and without warning symptoms. Elderly patients and patients with a prior history of peptic ulcer disease and/or GI bleeding are at greater risk for serious GI events (see WARNINGS).

DESCRIPTION

Naproxen is a proprionic acid derivative related to the arylacetic acid group of nonsteroidal anti-inflammatory drugs.

The chemical names for naproxen and naproxen sodium are (S)-6-methoxy-α-methyl-2-naphthaleneacetic acid and (S)-6-methoxy-α-methyl-2-naphthaleneacetic acid, sodium salt, respectively. Naproxen and naproxen sodium have the following structures, respectively:

Naproxen has a molecular weight of 230.26 and a molecular formula of C14H14O3. Naproxen sodium has a molecular weight of 252.23 and a molecular formula of C14H13NaO3.

Naproxen is an odorless, white to off-white crystalline substance. It is lipid-soluble, practically insoluble in water at low pH and freely soluble in water at high pH. The octanol/water partition coefficient of naproxen at pH 7.4 is 1.6 to 1.8. Naproxen sodium is a white to creamy white, crystalline solid, freely soluble in water at neutral pH.

NAPROXEN (naproxen tablets) is available as yellow tablets containing 250 mg of naproxen, pink tablets containing 375 mg of naproxen and yellow tablets containing 500 mg of naproxen for oral administration. The inactive ingredients are croscarmellose sodium, iron oxides, povidone and magnesium stearate.

EC-NAPROXEN (naproxen delayed-release tablets) is available as enteric-coated white tablets containing 375 mg of naproxen and 500 mg of naproxen for oral administration. The inactive ingredients are croscarmellose sodium, povidone and magnesium stearate. The enteric coating dispersion contains methacrylic acid copolymer, talc, triethyl citrate, sodium hydroxide and purified water. The dissolution of this enteric-coated naproxen tablet is pH dependent with rapid dissolution above pH 6. There is no dissolution below pH 4.

NAPROXEN SODIUM (naproxen sodium tablets) is available as blue tablets containing 275 mg of naproxen sodium and NAPROXEN SODIUM DS (naproxen sodium tablets) is available as dark blue tablets containing 550 mg of naproxen sodium for oral administration. The inactive ingredients are magnesium stearate, microcrystalline cellulose, povidone and talc. The coating suspension for the NAPROXEN SODIUM 275 mg tablet may contain hydroxypropyl methylcellulose 2910, Opaspray K-1-4210A, polyethylene glycol 8000 or Opadry YS-1-4215. The coating suspension for the NAPROXEN SODIUM DS 550 mg tablet may contain hydroxypropyl methylcellulose 2910, Opaspray K-1-4227, polyethylene glycol 8000 or Opadry YS-1-4216.

CLINICAL PHARMACOLOGY

Mechanism of Action

Naproxen has analgesic, anti-inflammatory, and antipyretic properties. The sodium salt of naproxen has been developed as a more rapidly absorbed formulation of naproxen for use as an analgesic.

The mechanism of action of the naproxen, like that of other NSAIDs, is not completely understood but involves inhibition of cyclooxygenase (COX-1 and COX-2).

Naproxen is a potent inhibitor of prostaglandin synthesis in vitro. Naproxen concentrations reached during therapy have produced in vivo effects. Prostaglandins sensitize afferent nerves and potentiate the action of bradykinin in inducing pain in animal models. Prostaglandins are mediators of inflammation. Because naproxen is an inhibitor of prostaglandin synthesis, its mode of action may be due to a decrease of prostaglandins in peripheral tissues.

Pharmacokinetics

Naproxen and naproxen sodium are rapidly and completely absorbed from the gastrointestinal tract with an in vivo bioavailability of 95%. The different dosage forms of NAPROXEN are bioequivalent in terms of extent of absorption (AUC) and peak concentration (Cmax); however, the products do differ in their pattern of absorption. These differences between naproxen products are related to both the chemical form of naproxen used and its formulation. Even with the observed differences in pattern of absorption, the elimination half-life of naproxen is unchanged across products ranging from 12 to 17 hours. Steady-state levels of naproxen are reached in 4 to 5 days, and the degree of naproxen accumulation is consistent with this half-life. This suggests that the differences in pattern of release play only a negligible role in the attainment of steady-state plasma levels.

Absorption

NAPROXEN

After administration of NAPROXEN tablets, peak plasma levels are attained in 2 to 4 hours. After oral administration of ANAPROX, peak plasma levels are attained in 1 to 2 hours. The difference in rates between the two products is due to the increased aqueous solubility of the sodium salt of naproxen used in ANAPROX. Peak plasma levels of naproxen given as NAPROXEN Suspension are attained in 1 to 4 hours.

EC-NAPROXEN

EC-NAPROXEN is designed with a pH-sensitive coating to provide a barrier to disintegration in the acidic environment of the stomach and to lose integrity in the more neutral environment of the small intestine. The enteric polymer coating selected for EC-NAPROXEN dissolves above pH 6. When EC-NAPROXEN was given to fasted subjects, peak plasma levels were attained about 4 to 6 hours following the first dose (range: 2 to 12 hours). An in vivo study in man using radiolabeled EC-NAPROXEN tablets demonstrated that EC-NAPROXEN dissolves primarily in the small intestine rather than in the stomach, so the absorption of the drug is delayed until the stomach is emptied.

When EC-NAPROXEN and NAPROXEN were given to fasted subjects (n=24) in a crossover study following 1 week of dosing, differences in time to peak plasma levels (Tmax) were observed, but there were no differences in total absorption as measured by Cmax and AUC:

 | EC-NAPROXEN* 500 mg bid | EC-NAPROXEN* 500 mg bid
Cmax (µg/mL) | 94.9 (18%) | 97.4 (13%)
Tmax (hours) | 4 (39%) | 1.9 (61%)
AUC0–12 hr (µg·hr/mL) | 845 (20%) | 767 (15%)

*Mean value (coefficient of variation)

Antacid Effects
When EC-NAPROXEN was given as a single dose with antacid (54 mEq buffering capacity), the peak plasma levels of naproxen were unchanged, but the time to peak was reduced (mean Tmax fasted 5.6 hours, mean Tmax with antacid 5 hours), although not significantly. (see PRECAUTIONS; Drug Interactions).

Food Effects
When EC-NAPROXEN was given as a single dose with food, peak plasma levels in most subjects were achieved in about 12 hours (range: 4 to 24 hours). Residence time in the small intestine until disintegration was independent of food intake. The presence of food prolonged the time the tablets remained in the stomach, time to first detectable serum naproxen levels, and time to maximal naproxen levels (Tmax), but did not affect peak naproxen levels (Cmax).

Distribution

Naproxen has a volume of distribution of 0.16 L/kg. At therapeutic levels naproxen is greater than 99% albumin-bound. At doses of naproxen greater than 500 mg/day there is less than proportional increase in plasma levels due to an increase in clearance caused by saturation of plasma protein binding at higher doses (average trough Css 36.5, 49.2 and 56.4 mg/L with 500, 1000 and 1500 mg daily doses of naproxen, respectively). The naproxen anion has been found in the milk of lactating women at a concentration equivalent to approximately 1% of maximum naproxen concentration in plasma (see PRECAUTIONS: Nursing Mothers).

Elimination

Metabolism
Naproxen is extensively metabolized in the liver to 6-0-desmethyl naproxen, and both parent and metabolites do not induce metabolizing enzymes. Both naproxen and 6-0-desmethyl naproxen are further metabolized to their respective acylglucuronide conjugated metabolites.

Excretion
The clearance of naproxen is 0.13 mL/min/kg. Approximately 95% of the naproxen from any dose is excreted in the urine, primarily as naproxen (<1%), 6-0-desmethyl naproxen (<1%) or their conjugates (66% to 92%). The plasma half-life of the naproxen anion in humans ranges from 12 to 17 hours. The corresponding half-lives of both naproxen’s metabolites and conjugates are shorter than 12 hours, and their rates of excretion have been found to coincide closely with the rate of naproxen disappearance from the plasma. Small amounts, 3% or less of the administered dose, are excreted in the feces. In patients with renal failure metabolites may accumulate (see WARNINGS; Renal Toxicity and Hyperkalemia).

Special Populations

Pediatric Patients
In pediatric patients aged 5 to 16 years with arthritis, plasma naproxen levels following a 5 mg/kg single dose of naproxen suspension (see DOSAGE AND ADMINISTRATION) were found to be similar to those found in normal adults following a 500 mg dose. The terminal half-life appears to be similar in pediatric and adult patients. Pharmacokinetic studies of naproxen were not performed in pediatric patients younger than 5 years of age. Pharmacokinetic parameters appear to be similar following administration of naproxen suspension or tablets in pediatric patients. EC-NAPROXEN has not been studied in subjects under the age of 18.

Geriatric Patients
Studies indicate that although total plasma concentration of naproxen is unchanged, the unbound plasma fraction of naproxen is increased in the elderly, although the unbound fraction is <1% of the total naproxen concentration. Unbound trough naproxen concentrations in elderly subjects have been reported to range from 0.12% to 0.19% of total naproxen concentration, compared with 0.05% to 0.075% in younger subjects. The clinical significance of this finding is unclear, although it is possible that the increase in free naproxen concentration could be associated with an increase in the rate of adverse events per a given dosage in some elderly patients.

Race
Pharmacokinetic differences due to race have not been studied.

Hepatic Impairment
Naproxen pharmacokinetics has not been determined in subjects with hepatic insufficiency.

Chronic alcoholic liver disease and probably other diseases with decreased or abnormal plasma proteins (albumin) reduce the total plasma concentration of naproxen, but the plasma concentration of unbound naproxen is increased. Caution is advised when high doses are required and some adjustment of dosage may be required in these patients. It is prudent to use the lowest effective dose.

Renal Impairment

Naproxen pharmacokinetics has not been determined in subjects with renal insufficiency. Given that naproxen, its metabolites and conjugates are primarily excreted by the kidney, the potential exists for naproxen metabolites to accumulate in the presence of renal insufficiency. Elimination of naproxen is decreased in patients with severe renal impairment. Naproxen-containing products are not recommended for use in patients with moderate to severe and severe renal impairment (creatinine clearance <30 mL/min) (see WARNINGS; Renal Toxicity and Hyperkalemia).

Drug Interaction Studies
Aspirin: When NSAIDs were administered with aspirin, the protein binding of NSAIDs were reduced, although the clearance of free NSAID was not altered. The clinical significance of this interaction is not known. See Table 1 for clinically significant drug interactions of NSAIDs with aspirin (see PRECAUTIONS: Drug Interactions).

CLINICAL STUDIES

General Information

Naproxen has been studied in patients with rheumatoid arthritis, osteoarthritis, juvenile arthritis, ankylosing spondylitis, tendonitis and bursitis, and acute gout. Improvement in patients treated for rheumatoid arthritis was demonstrated by a reduction in joint swelling, a reduction in duration of morning stiffness, a reduction in disease activity as assessed by both the investigator and patient, and by increased mobility as demonstrated by a reduction in walking time. Generally, response to naproxen has not been found to be dependent on age, sex, severity or duration of rheumatoid arthritis.

In patients with osteoarthritis, the therapeutic action of naproxen has been shown by a reduction in joint pain or tenderness, an increase in range of motion in knee joints, increased mobility as demonstrated by a reduction in walking time, and improvement in capacity to perform activities of daily living impaired by the disease.

In a clinical trial comparing standard formulations of naproxen 375 mg bid (750 mg a day) vs 750 mg bid (1500 mg/day), 9 patients in the 750 mg group terminated prematurely because of adverse events. Nineteen patients in the 1500 mg group terminated prematurely because of adverse events. Most of these adverse events were gastrointestinal events.

In clinical studies in patients with rheumatoid arthritis, osteoarthritis, and juvenile arthritis, naproxen has been shown to be comparable to aspirin and indomethacin in controlling the aforementioned measures of disease activity, but the frequency and severity of the milder gastrointestinal adverse effects (nausea, dyspepsia, heartburn) and nervous system adverse effects (tinnitus, dizziness, lightheadedness) were less in naproxen-treated patients than in those treated with aspirin or indomethacin.

In patients with ankylosing spondylitis, naproxen has been shown to decrease night pain, morning stiffness and pain at rest. In double-blind studies the drug was shown to be as effective as aspirin, but with fewer side effects.

In patients with acute gout, a favorable response to naproxen was shown by significant clearing of inflammatory changes (eg, decrease in swelling, heat) within 24 to 48 hours, as well as by relief of pain and tenderness.

Naproxen has been studied in patients with mild to moderate pain secondary to postoperative, orthopedic, postpartum episiotomy and uterine contraction pain and dysmenorrhea. Onset of pain relief can begin within 1 hour in patients taking naproxen and within 30 minutes in patients taking naproxen sodium. Analgesic effect was shown by such measures as reduction of pain intensity scores, increase in pain relief scores, decrease in numbers of patients requiring additional analgesic medication, and delay in time to remedication. The analgesic effect has been found to last for up to 12 hours.

Naproxen may be used safely in combination with gold salts and/or corticosteroids; however, in controlled clinical trials, when added to the regimen of patients receiving corticosteroids, it did not appear to cause greater improvement over that seen with corticosteroids alone. Whether naproxen has a “steroid-sparing” effect has not been adequately studied. When added to the regimen of patients receiving gold salts, naproxen did result in greater improvement. Its use in combination with salicylates is not recommended because there is evidence that aspirin increases the rate of excretion of naproxen and data are inadequate to demonstrate that naproxen and aspirin produce greater improvement over that achieved with aspirin alone. In addition, as with other NSAIDs, the combination may result in higher frequency of adverse events than demonstrated for either product alone.

In ^51Cr blood loss and gastroscopy studies with normal volunteers, daily administration of 1000 mg of naproxen as 1000 mg of NAPROXEN or 1100 mg of naproxen sodium has been demonstrated to cause statistically significantly less gastric bleeding and erosion than 3250 mg of aspirin.

Three 6-week, double-blind, multicenter studies with EC-NAPROXEN (naproxen) (375 or 500 mg bid, n=385) and NAPROXEN (375 or 500 mg bid, n=279) were conducted comparing EC-NAPROXEN with NAPROXEN, including 355 rheumatoid arthritis and osteoarthritis patients who had a recent history of NSAID-related GI symptoms. These studies indicated that EC-NAPROXEN and NAPROXEN showed no significant differences in efficacy or safety and had similar prevalence of minor GI complaints. Individual patients, however, may find one formulation preferable to the other.

Five hundred and fifty-three patients received EC-NAPROXEN during long-term open-label trials (mean length of treatment was 159 days). The rates for clinically-diagnosed peptic ulcers and GI bleeds were similar to what has been historically reported for long-term NSAID use.

Geriatric Patients

The hepatic and renal tolerability of long-term naproxen administration was studied in two double-blind clinical trials involving 586 patients. Of the patients studied, 98 patients were age 65 and older and 10 of the 98 patients were age 75 and older. Naproxen was administered at doses of 375 mg twice daily or 750 mg twice daily for up to 6 months. Transient abnormalities of laboratory tests assessing hepatic and renal function were noted in some patients, although there were no differences noted in the occurrence of abnormal values among different age groups.

INDICATIONS AND USAGE

Carefully consider the potential benefits and risks of NAPROXEN, EC-NAPROXEN, ANAPROX, ANAPROX DS or NAPROXEN Suspension and other treatment options before deciding to use NAPROXEN, EC-NAPROXEN, NAPROXEN SODIUM or NAPROXEN SODIUM DS. Use the lowest effective dose for the shortest duration consistent with individual patient treatment goals (see WARNINGS: Gastrointestinal Bleeding, Ulceration, and Perforation).

Naproxen as NAPROXEN, EC-NAPROXEN, NAPROXEN SODIUM or NAPROXEN SODIUM DS is indicated:

- For the relief of the signs and symptoms of rheumatoid arthritis
- For the relief of the signs and symptoms of osteoarthritis
- For the relief of the signs and symptoms of ankylosing spondylitis
- For the relief of the signs and symptoms of juvenile arthritis

Naproxen as NAPROXEN Suspension is recommended for juvenile rheumatoid arthritis in order to obtain the maximum dosage flexibility based on the patient’s weight.

Naproxen as NAPROXEN, NAPROXEN SODIUM and NAPROXEN SODIUM DS is also indicated:

- For relief of the signs and symptoms of tendonitis
- For relief of the signs and symptoms of bursitis
- For relief of the signs and symptoms of acute gout
- For the management of pain
- For the management of primary dysmenorrhea

EC-NAPROXEN is not recommended for initial treatment of acute pain because the absorption of naproxen is delayed compared to absorption from other naproxen-containing products (see CLINICAL PHARMACOLOGY, DOSAGE AND ADMINISTRATION).

CONTRAINDICATIONS

NAPROXEN, EC-NAPROXEN, NAPROXEN SODIUM and NAPROXEN SODIUM DS are contraindicated in the following patients:

- Known hypersensitivity (e.g., anaphylactic reactions and serious skin reactions) to naproxen, naproxen sodium, or any components of the drug product (see WARNINGS; Anaphylactic Reactions, Serious Skin Reactions).
- History of asthma, urticaria, or other allergic-type reactions after taking aspirin or other NSAIDs. Severe, sometimes fatal, anaphylactic reactions to NSAIDs have been reported in such patients (see WARNINGS; Exacerbation of Asthma Related to Aspirin Sensitivity).
- In the setting of coronary artery bypass graft (CABG) surgery (see WARNINGS; Cardiovascular Thrombotic Events).

WARNINGS

Cardiovascular Thrombotic Events

Clinical trials of several COX-2 selective and nonselective NSAIDs of up to three years duration have shown an increased risk of serious cardiovascular (CV) thrombotic events, including myocardial infarction (MI) and stroke, which can be fatal. Based on available data, it is unclear that the risk for CV thrombotic events is similar for all NSAIDs. The relative increase in serious CV thrombotic events over baseline conferred by NSAID use appears to be similar in those with and without known CV disease or risk factors for CV disease. However, patients with known CV disease or risk factors had a higher absolute incidence of excess serious CV thrombotic events, due to their increased baseline rate. Some observational studies found that this increased risk of serious CV thrombotic events began as early as the first weeks of treatment. The increase in CV thrombotic risk has been observed most consistently at higher doses.

To minimize the potential risk for an adverse CV event in NSAID-treated patients, use the lowest effective dose for the shortest duration possible. Physicians and patients should remain alert for the development of such events, throughout the entire treatment course, even in the absence of previous CV symptoms. Patients should be informed about the symptoms of serious CV events and the steps to take if they occur.

There is no consistent evidence that concurrent use of aspirin mitigates the increased risk of serious CV thrombotic events associated with NSAID use. The concurrent use of aspirin and an NSAID, such as naproxen, increases the risk of serious gastrointestinal (GI) events (see WARNINGS: Gastrointestinal Bleeding, Ulceration, and Perforation).

Status Post Coronary Artery Bypass Graft (CABG) Surgery
Two large, controlled, clinical trials of a COX-2 selective NSAID for the treatment of pain in the first 10-14 days following CABG surgery found an increased incidence of myocardial infarction and stroke. NSAIDs are contraindicated in the setting of CABG (see CONTRAINDICATIONS).

Post-MI Patients
Observational studies conducted in the Danish National Registry have demonstrated that patients treated with NSAIDs in the post-MI period were at increased risk of reinfarction, CV-related death, and all-cause mortality beginning in the first week of treatment. In this same cohort, the incidence of death in the first year post-MI was 20 per 100 person years in NSAID-treated patients compared to 12 per 100 person years in non-NSAID exposed patients. Although the absolute rate of death declined somewhat after the first year post-MI, the increased relative risk of death in NSAID users persisted over at least the next four years of follow-up.

Avoid the use of NAPROXEN, EC-NAPROXEN, NAPROXEN SODIUM and NAPROXEN SODIUM DS in patients with a recent MI unless the benefits are expected to outweigh the risk of recurrent CV thrombotic events. If NAPROXEN, EC-NAPROXEN, NAPROXEN SODIUM or NAPROXEN SODIUM DS is used in patients with a recent MI, monitor patients for signs of cardiac ischemia.

Gastrointestinal Bleeding, Ulceration, and Perforation

NSAIDs, including naproxen cause serious gastrointestinal (GI) adverse events including inflammation, bleeding, ulceration, and perforation of the esophagus, stomach, small intestine, or large intestine, which can be fatal. These serious adverse events can occur at any time, with or without warning symptoms, in patients treated with NSAIDs. Only one in five patients who develop a serious upper GI adverse event on NSAID therapy is symptomatic. Upper GI ulcers, gross bleeding, or perforation caused by NSAIDs occurred in approximately 1% of patients treated for 3-6 months, and in about 2%-4% of patients treated for one year. However, even short-term NSAID therapy is not without risk.

Risk Factors for GI Bleeding, Ulceration, and Perforation

Patients with a prior history of peptic ulcer disease and/or GI bleeding who used NSAIDs had a greater than 10-fold increased risk for developing a GI bleed compared to patients without these risk factors. Other factors that increase the risk of GI bleeding in patients treated with NSAIDs include longer duration of NSAID therapy; concomitant use of oral corticosteroids, aspirin, anticoagulants, or selective serotonin reuptake inhibitors (SSRIs); smoking; use of alcohol; older age; and poor general health status. Most postmarketing reports of fatal GI events occurred in elderly or debilitated patients. Additionally, patients with advanced liver disease and/or coagulopathy are at increased risk for GI bleeding.

Strategies to Minimize the GI Risks in NSAID-treated patients:

- Use the lowest effective dosage for the shortest possible duration.
- Avoid administration of more than one NSAID at a time.
- Avoid use in patients at higher risk unless benefits are expected to outweigh the increased risk of bleeding. For such patients, as well as those with active GI bleeding, consider alternate therapies other than NSAIDs.
- Remain alert for signs and symptoms of GI ulceration and bleeding during NSAID therapy.
- If a serious GI adverse event is suspected, promptly initiate evaluation and treatment, and discontinue NAPROXEN, EC-NAPROXEN, NAPROXEN SODIUM or NAPROXEN SODIUM DS until a serious GI adverse event is ruled out.
- In the setting of concomitant use of low-dose aspirin for cardiac prophylaxis, monitor patients more closely for evidence of GI bleeding (see PRECAUTIONS; Drug Interactions).

Hepatotoxicity

Elevations of ALT or AST (three or more times the upper limit of normal [ULN]) have been reported in approximately 1% of patients in clinical trials. In addition, rare, sometimes fatal, cases of severe hepatic injury, including fulminant hepatitis, liver necrosis and hepatic failure have been reported.

Elevations of ALT or AST (less than three times ULN) may occur in up to 15% of patients taking NSAIDs including naproxen.

Inform patients of the warning signs and symptoms of hepatotoxicity (e.g., nausea, fatigue, lethargy, diarrhea, pruritus, jaundice, right upper quadrant tenderness, and "flu-like" symptoms). If clinical signs and symptoms consistent with liver disease develop, or if systemic manifestations occur (e.g., eosinophilia, rash, etc.), discontinue NAPROXEN, EC-NAPROXEN, NAPROXEN SODIUM or NAPROXEN SODIUM DS immediately, and perform a clinical evaluation of the patient.

Hypertension

NSAIDs, including NAPROXEN, EC-NAPROXEN, NAPROXEN SODIUM and NAPROXEN SODIUM DS, can lead to new onset of hypertension or worsening of preexisting hypertension, either of which may contribute to the increased incidence of CV events. Patients taking angiotensin converting enzyme (ACE) inhibitors, thiazide diuretics, or loop diuretics may have impaired response to these therapies when taking NSAIDs (see PRECAUTIONS; Drug Interactions).

Monitor blood pressure (BP) during the initiation of NSAID treatment and throughout the course of therapy.

Heart Failure and Edema

The Coxib and traditional NSAID Trialists’ Collaboration meta-analysis of randomized controlled trials demonstrated an approximately two-fold increase in hospitalization for heart failure in COX-2 selective-treated patients and nonselective NSAID-treated patients compared to placebo-treated patients. In a Danish National Registry study of patients with heart failure, NSAID use increased the risk of MI, hospitalization for heart failure, and death.

Additionally, fluid retention and edema have been observed in some patients treated with NSAIDs. Use of naproxen may blunt the CV effects of several therapeutic agents used to treat these medical conditions (e.g., diuretics, ACE inhibitors, or angiotensin receptor blockers [ARBs]) (see PRECAUTIONS; Drug Interactions).

Avoid the use of NAPROXEN, EC-NAPROXEN, NAPROXEN SODIUM and NAPROXEN SODIUM DS in patients with severe heart failure unless the benefits are expected to outweigh the risk of worsening heart failure. If NAPROXEN, EC-NAPROXEN, NAPROXEN SODIUM or NAPROXEN SODIUM DS is used in patients with severe heart failure, monitor patients for signs of worsening heart failure.

Since each NAPROXEN SODIUM or NAPROXEN SODIUM DS tablet contains 25 mg or 50 mg of sodium (about 1 mEq per each 250 mg of naproxen), this should be considered in patients whose overall intake of sodium must be severely restricted.

Renal Toxicity and Hyperkalemia

Renal Toxicity

Long-term administration of NSAIDs has resulted in renal papillary necrosis and other renal injury.

Renal toxicity has also been seen in patients in whom renal prostaglandins have a compensatory role in the maintenance of renal perfusion. In these patients, administration of an NSAID may cause a dose-dependent reduction in prostaglandin formation and, secondarily, in renal blood flow, which may precipitate overt renal decompensation. Patients at greatest risk of this reaction are those with impaired renal function, dehydration, hypovolemia, heart failure, liver dysfunction, those taking diuretics and ACE inhibitors or ARBs, and the elderly. Discontinuation of NSAID therapy is usually followed by recovery to the pretreatment state.

No information is available from controlled clinical studies regarding the use of NAPROXEN, EC-NAPROXEN, NAPROXEN SODIUM or NAPROXEN SODIUM DS in patients with advanced renal disease. The renal effects of NAPROXEN, EC-NAPROXEN, NAPROXEN SODIUM or NAPROXEN SODIUM DS may hasten the progression of renal dysfunction in patients with preexisting renal disease.

Correct volume status in dehydrated or hypovolemic patients prior to initiating NAPROXEN, EC-NAPROXEN, NAPROXEN SODIUM or NAPROXEN SODIUM DS. Monitor renal function in patients with renal or hepatic impairment, heart failure, dehydration, or hypovolemia during use of NAPROXEN, EC-NAPROXEN, NAPROXEN SODIUM or NAPROXEN SODIUM DS (see PRECAUTIONS; Drug Interactions). Avoid the use of NAPROXEN, EC-NAPROXEN, NAPROXEN SODIUM or NAPROXEN SODIUM DS in patients with advanced renal disease unless the benefits are expected to outweigh the risk of worsening renal function. If NAPROXEN, EC-NAPROXEN, NAPROXEN SODIUM or NAPROXEN SODIUM DS is used in patients with advanced renal disease, monitor patients for signs of worsening renal function.

Hyperkalemia
Increases in serum potassium concentration, including hyperkalemia, have been reported with use of NSAIDs, even in some patients without renal impairment. In patients with normal renal function, these effects have been attributed to a hyporeninemic-hypoaldosteronism state.

Anaphylactic Reactions

Naproxen has been associated with anaphylactic reactions in patients with and without known hypersensitivity to naproxen and in patients with aspirin-sensitive asthma (see CONTRAINDICATIONS, WARNINGS; Exacerbation of Asthma Related to Aspirin Sensitivity).

Exacerbation of Asthma Related to Aspirin Sensitivity

A subpopulation of patients with asthma may have aspirin-sensitive asthma which may include chronic rhinosinusitis complicated by nasal polyps; severe, potentially fatal bronchospasm; and/or intolerance to aspirin and other NSAIDs. Because cross-reactivity between aspirin and other NSAIDs has been reported in such aspirin-sensitive patients, NAPROXEN, EC-NAPROXEN, NAPROXEN SODIUM and NAPROXEN SODIUM DS are contraindicated in patients with this form of aspirin sensitivity (see CONTRAINDICATIONS). When NAPROXEN, EC-NAPROXEN, NAPROXEN SODIUM and NAPROXEN SODIUM DS are used in patients with preexisting asthma (without known aspirin sensitivity), monitor patients for changes in the signs and symptoms of asthma.

Serious Skin Reactions

NSAIDs, including naproxen, can cause serious skin adverse reactions such as exfoliative dermatitis, Stevens-Johnson Syndrome (SJS), and toxic epidermal necrolysis (TEN), which can be fatal. These serious events may occur without warning. Inform patients about the signs and symptoms of serious skin reactions and to discontinue the use of NAPROXEN, EC-NAPROXEN, NAPROXEN SODIUM or NAPROXEN SODIUM DS at the first appearance of skin rash or any other sign of hypersensitivity. NAPROXEN, EC-NAPROXEN, NAPROXEN SODIUM and NAPROXEN SODIUM DS are contraindicated in patients with previous serious skin reactions to NSAIDs (see CONTRAINDICATIONS).

Premature Closure of Fetal Ductus Arteriosus

Naproxen may cause premature closure of the fetal ductus arteriosus. Avoid use of NSAIDs, including NAPROXEN, EC-NAPROXEN, NAPROXEN SODIUM or NAPROXEN SODIUM DS, in pregnant women starting at 30 weeks of gestation (third trimester) (see PRECAUTIONS; Pregnancy).

Hematologic Toxicity

Anemia has occurred in NSAID-treated patients. This may be due to occult or gross blood loss, fluid retention, or an incompletely described effect on erythropoiesis. If a patient treated with NAPROXEN, EC-NAPROXEN, NAPROXEN SODIUM or NAPROXEN SODIUM DS has any signs or symptoms of anemia, monitor hemoglobin or hematocrit.

NSAIDs, including NAPROXEN, EC-NAPROXEN, NAPROXEN SODIUM or NAPROXEN SODIUM DS, may increase the risk of bleeding events. Co-morbid conditions such as coagulation disorders, or concomitant use of warfarin and other anticoagulants, antiplatelet agents (e.g., aspirin), serotonin reuptake inhibitors (SSRIs) and serotonin norepinephrine reuptake inhibitors (SNRIs) may increase this risk. Monitor these patients for signs of bleeding (see PRECAUTIONS; Drug Interactions).

PRECAUTIONS

General

Naproxen-containing products such as NAPROXEN, EC-NAPROXEN, NAPROXEN SODIUM and NAPROXEN SODIUM DS, and other naproxen products should not be used concomitantly since they all circulate in the plasma as the naproxen anion.

NAPROXEN, EC-NAPROXEN, NAPROXEN SODIUM and NAPROXEN SODIUM DS cannot be expected to substitute for corticosteroids or to treat corticosteroid insufficiency. Abrupt discontinuation of corticosteroids may lead to disease exacerbation. Patients on prolonged corticosteroid therapy should have their therapy tapered slowly if a decision is made to discontinue corticosteroids and the patient should be observed closely for any evidence of adverse effects, including adrenal insufficiency and exacerbation of symptoms of arthritis.

Patients with initial hemoglobin values of 10 g or less who are to receive long-term therapy should have hemoglobin values determined periodically.

Because of adverse eye findings in animal studies with drugs of this class, it is recommended that ophthalmic studies be carried out if any change or disturbance in vision occurs.

Information for Patients

Advise the patient to read the FDA-approved patient labeling (Medication Guide) that accompanies each prescription dispensed. Inform patients, families, or their caregivers of the following information before initiating therapy with NAPROXEN, EC-NAPROXEN, NAPROXEN SODIUM or NAPROXEN SODIUM DS and periodically during the course of ongoing therapy.

Cardiovascular Thrombotic Events
Advise patients to be alert for the symptoms of cardiovascular thrombotic events, including chest pain, shortness of breath, weakness, or slurring of speech, and to report any of these symptoms to their health care provider immediately (see WARNINGS; Cardiovascular Thrombotic Events).

Gastrointestinal Bleeding, Ulceration, and Perforation
Advise patients to report symptoms of ulcerations and bleeding, including epigastric pain, dyspepsia, melena, and hematemesis to their health care provider. In the setting of concomitant use of low-dose aspirin for cardiac prophylaxis, inform patients of the increased risk for the signs and symptoms of GI bleeding (see WARNINGS; Gastrointestinal Bleeding, Ulceration, and Perforation).

Hepatotoxicity
Inform patients of the warning signs and symptoms of hepatotoxicity (e.g., nausea, fatigue, lethargy, pruritus, jaundice, right upper quadrant tenderness, and “flu-like” symptoms). If these occur, instruct patients to stop NAPROXEN, EC-NAPROXEN, NAPROXEN SODIUM or NAPROXEN SODIUM DS and seek immediate medical therapy (see WARNINGS; Hepatotoxicity).

Heart Failure and Edema
Advise patients to be alert for the symptoms of congestive heart failure including shortness of breath, unexplained weight gain, or edema and to contact their healthcare provider if such symptoms occur (see WARNINGS; Heart Failure and Edema).

Anaphylactic Reactions
Inform patients of the signs of an anaphylactic reaction (e.g., difficulty breathing, swelling of the face or throat). Instruct patients to seek immediate emergency help if these occur (see CONTRAINDICATION, WARNINGS; Anaphylactic Reactions).

Serious Skin Reactions
Advise patients to stop NAPROXEN, EC-NAPROXEN, NAPROXEN SODIUM or NAPROXEN SODIUM DS immediately if they develop any type of rash and to contact their healthcare provider as soon as possible (see WARNINGS; Serious Skin Reactions).

Female Fertility
Advise females of reproductive potential who desire pregnancy that NSAIDs, including VOLTAREN, may be associated with a reversible delay in ovulation (see PRECAUTIONS; Carcinogenesis, Mutagenesis, Impairment of Fertility).

Fetal Toxicity
Inform pregnant women to avoid use of NAPROXEN, EC-NAPROXEN, NAPROXEN SODIUM, NAPROXEN SODIUM DS and other NSAIDs starting at 30 weeks gestation because of the risk of the premature closing of the fetal ductus arteriosus (see WARNINGS; Premature Closure of Fetal Ductus Arteriosus).

Avoid Concomitant Use of NSAIDs
Inform patients that the concomitant use of NAPROXEN, EC-NAPROXEN, NAPROXEN SODIUM and NAPROXEN SODIUM DS with other NSAIDs or salicylates (e.g., diflunisal, salsalate) is not recommended due to the increased risk of gastrointestinal toxicity, and little or no increase in efficacy (see WARNINGS;: Gastrointestinal Bleeding, Ulceration, and Perforation, PRECAUTIONS; Drug Interactions). Alert patients that NSAIDs may be present in “over the counter” medications for treatment of colds, fever, or insomnia.

Use of NSAIDS and Low-Dose Aspirin
Inform patients not to use low-dose aspirin concomitantly with NAPROXEN, EC-NAPROXEN, NAPROXEN SODIUM and NAPROXEN SODIUM DS until they talk to their healthcare provider (see PRECAUTIONS; Drug Interactions).

Activities Requiring Alertness
Caution should be exercised by patients whose activities require alertness if they experience drowsiness, dizziness, vertigo or depression during therapy with naproxen.

Masking of Inflammation and Fever

The pharmacological activity of NAPROXEN, EC-NAPROXEN, NAPROXEN SODIUM or NAPROXEN SODIUM DS in reducing inflammation, and possibly fever, may diminish the utility of diagnostic signs in detecting infections.

Laboratory Monitoring

Because serious GI bleeding, hepatotoxicity, and renal injury can occur without warning symptoms or signs, consider monitoring patients on long-term NSAID treatment with a CBC and a chemistry profile periodically (see WARNINGS; Gastrointestinal Bleeding, Ulceration, and Perforation, and Hepatotoxicity).

Drug Interactions

See Table 1 for clinically significant drug interactions with naproxen.

Table 1: Clinically Significant Drug Interactions with naproxen
Drugs That Interfere with Hemostasis
Clinical Impact: | • Naproxen and anticoagulants such as warfarin have a synergistic effect on bleeding. The concomitant use of naproxen and anticoagulants has an increased risk of serious bleeding compared to the use of either drug alone. • Serotonin release by platelets plays an important role in hemostasis. Case-control and cohort epidemiological studies showed that concomitant use of drugs that interfere with serotonin reuptake and an NSAID may potentiate the risk of bleeding more than an NSAID alone. Monitor patients with concomitant use of NAPROXEN, EC-NAPROXEN, NAPROXEN SODIUM or NAPROXEN SODIUM DS with anticoagulants (e.g., warfarin), antiplatelet agents (e.g., aspirin), selective serotonin reuptake inhibitors (SSRIs), and serotonin norepinephrine reuptake inhibitors (SNRIs) for signs of bleeding (see WARNINGS; Hematologic Toxicity).
Intervention: | Monitor patients with concomitant use of NAPROXEN, EC-NAPROXEN, NAPROXEN SODIUM or NAPROXEN SODIUM DS with anticoagulants (e.g., warfarin), antiplatelet agents (e.g., aspirin), selective serotonin reuptake inhibitors (SSRIs), and serotonin norepinephrine reuptake inhibitors (SNRIs) for signs of bleeding (see WARNINGS; Hematologic Toxicity).
Aspirin
Clinical Impact: | Controlled clinical studies showed that the concomitant use of NSAIDs and analgesic doses of aspirin does not produce any greater therapeutic effect than the use of NSAIDs alone. In a clinical study, the concomitant use of an NSAID and aspirin was associated with a significantly increased incidence of GI adverse reactions as compared to use of the NSAID alone (see WARNINGS; Gastrointestinal Bleeding, Ulceration, and Perforation).
Intervention: | Concomitant use of NAPROXEN, EC- NAPROXEN, NAPROXEN SODIUM or NAPROXEN SODIUM DS and analgesic doses of aspirin is not generally recommended because of the increased risk of bleeding (see WARNINGS; Hematologic Toxicity). NAPROXEN, EC-NAPROXEN, NAPROXEN SODIUM or NAPROXEN SODIUM DS is not a substitute for low dose aspirin for cardiovascular protection.
ACE Inhibitors, Angiotensin Receptor Blockers, and Beta-Blockers
Clinical Impact: | • NSAIDs may diminish the antihypertensive effect of angiotensin converting enzyme (ACE) inhibitors, angiotensin receptor blockers (ARBs), or beta-blockers (including propranolol). • In patients who are elderly, volume-depleted (including those on diuretic therapy), or have renal impairment, co-administration of an NSAID with ACE inhibitors or ARBs may result in deterioration of renal function, including possible acute renal failure. These effects are usually reversible.
Intervention: | • During concomitant use of NAPROXEN, EC-NAPROXEN, NAPROXEN SODIUM or NAPROXEN SODIUM DS and ACE-inhibitors, ARBs, or beta-blockers, monitor blood pressure to ensure that the desired blood pressure is obtained. • During concomitant use of NAPROXEN, EC-NAPROXEN, NAPROXEN SODIUM or NAPROXEN SODIUM DS and ACE-inhibitors or ARBs in patients who are elderly, volume-depleted, or have impaired renal function, monitor for signs of worsening renal function (see WARNINGS; Renal Toxicity and Hyperkalemia). When these drugs are administered concomitantly, patients should be adequately hydrated. Assess renal function at the beginning of the concomitant treatment and periodically thereafter.
Diuretics
Clinical Impact: | Clinical studies, as well as post-marketing observations, showed that NSAIDs reduced the natriuretic effect of loop diuretics (e.g., furosemide) and thiazide diuretics in some patients. This effect has been attributed to the NSAID inhibition of renal prostaglandin synthesis.
Intervention: | During concomitant use of NAPROXEN, EC-NAPROXEN, NAPROXEN SODIUM or NAPROXEN SODIUM DS with diuretics, observe patients for signs of worsening renal function, in addition to assuring diuretic efficacy including antihypertensive effects (see WARNINGS; Renal Toxicity and Hyperkalemia).
Digoxin
Clinical Impact: | The concomitant use of naproxen with digoxin has been reported to increase the serum and prolong the half-life of digoxin.
Intervention: | During concomitant use of NAPROXEN, EC-NAPROXEN, NAPROXEN SODIUM or NAPROXEN SODIUM DS and digoxin, monitor serum digoxin levels.
Lithium
Clinical Impact: | NSAIDs have produced elevations in plasma lithium levels and reductions in renal lithium clearance. The mean minimum lithium concentration increased 15%, and the renal clearance decreased by approximately 20%. This effect has been attributed to NSAID inhibition of renal prostaglandin synthesis.
Intervention: | During concomitant use of NAPROXEN, EC-NAPROXEN, NAPROXEN SODIUM or NAPROXEN SODIUM DS and lithium, monitor patients for signs of lithium toxicity.
Methotrexate
Clinical Impact: | Concomitant use of NSAIDs and methotrexate may increase the risk for methotrexate toxicity (e.g., neutropenia, thrombocytopenia, renal dysfunction).
Intervention: | During concomitant use of NAPROXEN, EC-NAPROXEN, NAPROXEN SODIUM or NAPROXEN SODIUM DS and methotrexate, monitor patients for methotrexate toxicity.
Cyclosporine
Clinical Impact: | Concomitant use of NAPROXEN, EC-NAPROXEN, NAPROXEN SODIUM or NAPROXEN SODIUMDS and cyclosporine may increase cyclosporine’s nephrotoxicity.
Intervention: | During concomitant use of NAPROXEN, EC-NAPROXEN, NAPROXEN SODIUM or NAPROXEN SODIUM DS and cyclosporine, monitor patients for signs of worsening renal function.
NSAIDs and Salicylates
Clinical Impact: | Concomitant use of naproxen with other NSAIDs or salicylates (e.g., diflunisal, salsalate) increases the risk of GI toxicity, with little or no increase in efficacy (see WARNINGS; Gastrointestinal Bleeding, Ulceration and Perforation).
Intervention: | The concomitant use of naproxen with other NSAIDs or salicylates is not recommended.
Pemetrexed
Clinical Impact: | Concomitant use of NAPROXEN, EC-NAPROXEN, NAPROXEN SODIUM or NAPROXEN SODIUM DS and pemetrexed may increase the risk of pemetrexed-associated myelosuppression, renal, and GI toxicity (see the pemetrexed prescribing information).
Intervention: | During concomitant use of NAPROXEN, EC-NAPROXEN, NAPROXEN SODIUM or NAPROXEN SODIUM DS and pemetrexed, in patients with renal impairment whose creatinine clearance ranges from 45 to 79 mL/min, monitor for myelosuppression, renal and GI toxicity. NSAIDs with short elimination half-lives (e.g., diclofenac, indomethacin) should be avoided for a period of two days before, the day of, and two days following administration of pemetrexed. In the absence of data regarding potential interaction between pemetrexed and NSAIDs with longer half-lives (e.g., meloxicam, nabumetone), patients taking these NSAIDs should interrupt dosing for at least five days before, the day of, and two days following pemetrexed administration.
Antacids and Sucralfate
Clinical Impact: | Concomitant administration of some antacids (magnesium oxide or aluminum hydroxide) and sucralfate can delay the absorption of naproxen.
Intervention: | Concomitant administration of antacids such as magnesium oxide or aluminum hydroxide, and sucralfate with NAPROXEN, EC-NAPROXEN, NAPROXEN SODIUM or NAPROXEN SODIUM DS is not recommended. Due to the gastric pH elevating effects of H2-blockers, sucralfate and intensive antacid therapy, concomitant administration of EC-NAPROXEN is not recommended.
Cholestyramine
Clinical Impact: | Concomitant administration of cholestyramine can delay the absorption of naproxen.
Intervention: | Concomitant administration of cholestyramine with NAPROXEN, EC-NAPROXEN, NAPROXEN SODIUM or NAPROXEN SODIUM DS is not recommended.
Probenecid
Clinical Impact: | Probenecid given concurrently increases naproxen anion plasma levels and extends its plasma half-life significantly.
Intervention: | Patients simultaneously receiving NAPROXEN, EC-NAPROXEN, NAPROXEN SODIUM or NAPROXEN SODIUM DS and probenecid should be observed for adjustment of dose if required.
Other albumin-bound drugs
Clinical Impact: | Naproxen is highly bound to plasma albumin; it thus has a theoretical potential for interaction with other albumin-bound drugs such as coumarin-type anticoagulants, sulphonylureas, hydantoins, other NSAIDs, and aspirin.
Intervention: | Patients simultaneously receiving NAPROXEN, EC-NAPROXEN, NAPROXEN SODIUM or NAPROXEN SODIUM DS and a hydantoin, sulphonamide or sulphonylurea should be observed for adjustment of dose if required.

Drug/Laboratory Test Interactions
Bleeding times
Clinical Impact: | Naproxen may decrease platelet aggregation and prolong bleeding time.
Intervention: | This effect should be kept in mind when bleeding times are determined.
Porter-Silber test
Clinical Impact: | The administration of naproxen may result in increased urinary values for 17-ketogenic steroids because of an interaction between the drug and/or its metabolites with m-di-nitrobenzene used in this assay.
Intervention: | Although 17-hydroxy-corticosteroid measurements (Porter-Silber test) do not appear to be artifactually altered, it is suggested that therapy with naproxen be temporarily discontinued 72 hours before adrenal function tests are performed if the Porter-Silber test is to be used.
Urinary assays of 5-hydroxy indoleacetic acid (5HIAA)
Clinical Impact: | Naproxen may interfere with some urinary assays of 5-hydroxy indoleacetic acid (5HIAA).
Intervention: | This effect should be kept in mind when urinary 5-hydroxy indoleacetic acid is determined.

Carcinogenesis, Mutagenesis, Impairment of Fertility

Carcinogenesis
A 2-year study was performed in rats to evaluate the carcinogenic potential of naproxen at rat doses t of 8, 16, and 24 mg/kg/day (0.05, 0.1, and 0.16 times the maximum recommended human daily dose [MRHD] of 1500 mg/day based on a body surface area comparison). No evidence of tumorigenicity was found.

Mutagenesis
Studies to evaluate the mutagenic potential of Naproxen, EC-Naproxen, Naproxen Sodium or Naproxen Sodium DS tablets have not been completed.

Impairment of fertility
Male rats were treated with 2, 5, 10, and 20 mg/kg naproxen by oral gavage for 60 days prior to mating and female rats were treated with the same doses for 14 days prior to mating and for the first 7 days of pregnancy. There were no adverse effects on fertility noted (up to 0.13 times the MRDH based on body surface area).

Pregnancy

Risk Summary
Use of NSAIDs, including Naproxen, EC-Naproxen, Naproxen Sodium, and Naproxen Sodium DS tablets, during the third trimester of pregnancy increases the risk of premature closure of the fetal ductus arteriosus. Avoid use of NSAIDs, including Naproxen, in pregnant women starting at 30 weeks of gestation (third trimester) (see WARNINGS; Premature Closure of Fetal Ductus Arteriosus).

There are no adequate and well-controlled studies of Naproxen, EC-Naproxen, Naproxen Sodium, or Naproxen Sodium DS tablets in pregnant women.

Data from observational studies regarding potential embryofetal risks of NSAID use in women in the first or second trimesters of pregnancy are inconclusive. In the general U.S. population, all clinically recognized pregnancies, regardless of drug exposure, have a background rate of 2-4% for major malformations, and 15-20% for pregnancy loss. In animal reproduction studies in rats, rabbit, and mice no evidence of teratogenicity or fetal harm when naproxen was administered during the period of organogenesis at doses 0.13, 0.26, and 0.6 times the maximum recommended human daily dose of 1500 mg/day, respectively. Based on animal data, prostaglandins have been shown to have an important role in endometrial vascular permeability, blastocyst implantation, and decidualization. In animal studies, administration of prostaglandin synthesis inhibitors such as naproxen, resulted in increased pre- and post-implantation loss.

Data
Human Data
There is some evidence to suggest that when inhibitors of prostaglandin synthesis are used to delay preterm labor there is an increased risk of neonatal complications such as necrotizing enterocolitis, patent ductus arteriosus and intracranial hemorrhage. Naproxen treatment given in late pregnancy to delay parturition has been associated with persistent pulmonary hypertension, renal dysfunction and abnormal prostaglandin E levels in preterm infants. Because of the known effects of nonsteroidal anti-inflammatory drugs on the fetal cardiovascular system (closure of ductus arteriosus), use during pregnancy (particularly starting at 30-weeks of gestation, or third trimester) should be avoided.

Animal Data
Reproduction studies have been performed in rats at 20 mg/kg/day (0.13 times the maximum recommended human daily dose of 1500 mg/day based on body surface area comparison), rabbits at 20 mg/kg/day (0.26 times the maximum recommended human daily dose, based on body surface area comparison), and mice at 170 mg/kg/day (0.6 times the maximum recommended human daily dose based on body surface area comparison) with no evidence of impaired fertility or harm to the fetus due to the drug. Based on animal data, prostaglandins have been shown to have an important role in endometrial vascular permeability, blastocyst implantation, and decidualization. In animal studies, administration of prostaglandin synthesis inhibitors such as naproxen, resulted in increased pre- and post-implantation loss.

Labor and Delivery

There are no studies on the effects of Naproxen, EC-Naproxen, Naproxen Sodium or Naproxen Sodium DS tablets during labor or delivery. In animal studies, NSAIDS, including naproxen, inhibit prostaglandin synthesis, cause delayed parturition, and increase the incidence of stillbirth.

Nursing Mothers

The naproxen anion has been found in the milk of lactating women at a concentration equivalent to approximately 1% of maximum naproxen concentration in plasma. The developmental and health benefits of breastfeeding should be considered along with the mother’s clinical need for Naproxen, EC-Naproxen, Naproxen Sodium, or Naproxen Sodium DS tablets and any potential adverse effects on the breastfed infant from the Naproxen, EC-Naproxen, Naproxen Sodium, or Naproxen Sodium DS tablets or from the underlying maternal condition.

Females and Males of Reproductive Potential

Based on the mechanism of action, the use of prostaglandin-mediated NSAIDs, including Naproxen, may delay or prevent rupture of ovarian follicles, which has been associated with reversible infertility in some women. Published animal studies have shown that administration of prostaglandin synthesis inhibitors has the potential to disrupt prostaglandin-mediated follicular rupture required for ovulation. Small studies in women treated with NSAIDs have also shown a reversible delay in ovulation.
Consider withdrawal of NSAIDs, including Naproxen, EC-Naproxen, Naproxen Sodium and Naproxen Sodium DS tablets, in women who have difficulties conceiving or who are undergoing investigation of infertility.

Pediatric Use

Safety and effectiveness in pediatric patients below the age of 2 years have not been established. Pediatric dosing recommendations for juvenile arthritis are based on well-controlled studies (see DOSAGE AND ADMINISTRATION). There are no adequate effectiveness or dose-response data for other pediatric conditions, but the experience in juvenile arthritis and other use experience have established that single doses of 2.5 to 5 mg/kg (as naproxen suspension, see DOSAGE AND ADMINISTRATION), with total daily dose not exceeding 15 mg/kg/day, are well tolerated in pediatric patients over 2 years of age.

Geriatric Use

Elderly patients, compared to younger patients, are at greater risk for NSAID-associated serious cardiovascular, gastrointestinal, and/or renal adverse reactions. If the anticipated benefit for the elderly patient outweighs these potential risks, start dosing at the low end of the dosing range, and monitor patients for adverse effects (see WARNINGS; Cardiovascular Thrombotic Events, Gastrointestinal Bleeding, Ulceration, and Perforation, Hepatotoxicity, Renal Toxicity and Hyperkalemia, PRECAUTIONS; Laboratory Monitoring).

Studies indicate that although total plasma concentration of naproxen is unchanged, the unbound plasma fraction of naproxen is increased in the elderly. Caution is advised when high doses are required and some adjustment of dosage may be required in elderly patients. As with other drugs used in the elderly, it is prudent to use the lowest effective dose.

Experience indicates that geriatric patients may be particularly sensitive to certain adverse effects of nonsteroidal anti-inflammatory drugs. Elderly or debilitated patients seem to tolerate peptic ulceration or bleeding less well when these events do occur. Most spontaneous reports of fatal GI events are in the geriatric population (see WARNINGS; Gastrointestinal Bleeding, Ulceration, and Perforation).

Naproxen is known to be substantially excreted by the kidney, and the risk of toxic reactions to this drug may be greater in patients with impaired renal function. Because elderly patients are more likely to have decreased renal function, care should be taken in dose selection, and it may be useful to monitor renal function. Geriatric patients may be at a greater risk for the development of a form of renal toxicity precipitated by reduced prostaglandin formation during administration of nonsteroidal anti-inflammatory drugs (see WARNINGS: Renal Toxicity and Hyperkalemia).

ADVERSE REACTIONS

The following adverse reactions are discussed in greater detail in other sections of the labeling:

- Cardiovascular Thrombotic Events (see WARNINGS)
- GI Bleeding, Ulceration and Perforation (see WARNINGS)
- Hepatotoxicity (see WARNINGS)
- Hypertension (see WARNINGS)
- Heart Failure and Edema (see WARNINGS)
- Renal Toxicity and Hyperkalemia (see WARNINGS)
- Anaphylactic Reactions (see WARNINGS)
- Serious Skin Reactions (see WARNINGS)
- Hematologic Toxicity (see WARNINGS)

Adverse reactions reported in controlled clinical trials in 960 patients treated for rheumatoid arthritis or osteoarthritis are listed below. In general, reactions in patients treated chronically were reported 2 to 10 times more frequently than they were in short-term studies in the 962 patients treated for mild to moderate pain or for dysmenorrhea. The most frequent complaints reported related to the gastrointestinal tract.

A clinical study found gastrointestinal reactions to be more frequent and more severe in rheumatoid arthritis patients taking daily doses of 1500 mg naproxen compared to those taking 750 mg naproxen (see CLINICAL PHARMACOLOGY).

In controlled clinical trials with about 80 pediatric patients and in well-monitored, open-label studies with about 400 pediatric patients with juvenile arthritis treated with naproxen, the incidence of rash and prolonged bleeding times were increased, the incidence of gastrointestinal and central nervous system reactions were about the same, and the incidence of other reactions were lower in pediatric patients than in adults.

In patients taking naproxen in clinical trials, the most frequently reported adverse experiences in approximately 1% to 10% of patients are:

Gastrointestinal (GI) Experiences, including: heartburn*, abdominal pain*, nausea*, constipation*, diarrhea, dyspepsia, stomatitis

Central Nervous System: headache*, dizziness*, drowsiness*, lightheadedness, vertigo

Dermatologic: pruritus (itching)*, skin eruptions*, ecchymoses*, sweating, purpura

Special Senses: tinnitus*, visual disturbances, hearing disturbances

Cardiovascular: edema*, palpitations

General: dyspnea*, thirst

*Incidence of reported reaction between 3% and 9%. Those reactions occurring in less than 3% of the patients are unmarked.

In patients taking NSAIDs, the following adverse experiences have also been reported in approximately 1% to 10% of patients.

Gastrointestinal (GI) Experiences, including: flatulence, gross bleeding/perforation, GI ulcers (gastric/duodenal), vomiting

General: abnormal renal function, anemia, elevated liver enzymes, increased bleeding time, rashes

The following are additional adverse experiences reported in <1% of patients taking naproxen during clinical trials and through postmarketing reports. Those adverse reactions observed through postmarketing reports are italicized.

Body as a Whole: anaphylactoid reactions, angioneurotic edema, menstrual disorders, pyrexia (chills and fever)

Cardiovascular: congestive heart failure, vasculitis, hypertension, pulmonary edema

Gastrointestinal: inflammation, bleeding (sometimes fatal, particularly in the elderly), ulceration, perforation and obstruction of the upper or lower gastrointestinal tract. Esophagitis, stomatitis, hematemesis, pancreatitis, vomiting, colitis, exacerbation of inflammatory bowel disease (ulcerative colitis, Crohn’s disease).

Hepatobiliary: jaundice, abnormal liver function tests, hepatitis (some cases have been fatal)

Hemic and Lymphatic: eosinophilia, leucopenia, melena, thrombocytopenia, agranulocytosis, granulocytopenia, hemolytic anemia, aplastic anemia

Metabolic and Nutritional: hyperglycemia, hypoglycemia

Nervous System: inability to concentrate, depression, dream abnormalities, insomnia, malaise, myalgia, muscle weakness, aseptic meningitis, cognitive dysfunction, convulsions

Respiratory: eosinophilic pneumonitis, asthma

Dermatologic: alopecia, urticaria, skin rashes, toxic epidermal necrolysis, erythema multiforme, erythema nodosum, fixed drug eruption, lichen planus, pustular reaction, systemic lupus erythematoses, bullous reactions, including Stevens-Johnson syndrome, photosensitive dermatitis, photosensitivity reactions, including rare cases resembling porphyria cutanea tarda (pseudoporphyria) or epidermolysis bullosa. If skin fragility, blistering or other symptoms suggestive of pseudoporphyria occur, treatment should be discontinued and the patient monitored.

Special Senses: hearing impairment, corneal opacity, papillitis, retrobulbar optic neuritis, papilledema

Urogenital: glomerular nephritis, hematuria, hyperkalemia, interstitial nephritis, nephrotic syndrome, renal disease, renal failure, renal papillary necrosis, raised serum creatinine

Reproduction (female): infertility

In patients taking NSAIDs, the following adverse experiences have also been reported in <1% of patients.

Body as a Whole: fever, infection, sepsis, anaphylactic reactions, appetite changes, death

Cardiovascular: hypertension, tachycardia, syncope, arrhythmia, hypotension, myocardial infarction

Gastrointestinal: dry mouth, esophagitis, gastric/peptic ulcers, gastritis, glossitis, eructation

Hepatobiliary: hepatitis, liver failure

Hemic and Lymphatic: rectal bleeding, lymphadenopathy, pancytopenia

Metabolic and Nutritional: weight changes

Nervous System: anxiety, asthenia, confusion, nervousness, paresthesia, somnolence, tremors, convulsions, coma, hallucinations

Respiratory: asthma, respiratory depression, pneumonia

Dermatologic: exfoliative dermatitis

Special Senses: blurred vision, conjunctivitis

Urogenital: cystitis, dysuria, oliguria/polyuria, proteinuria

OVERDOSAGE

Symptoms and Signs

Symptoms following acute NSAID overdosages have been typically limited to lethargy, drowsiness, nausea, vomiting, and epigastric pain, which have been generally reversible with supportive care. Gastrointestinal bleeding has occurred. Hypertension, acute renal failure, respiratory depression, and coma have occurred, but were rare. Because naproxen sodium may be rapidly absorbed, high and early blood levels should be anticipated. A few patients have experienced convulsions, but it is not clear whether or not these were drug-related. It is not known what dose of the drug would be life threatening. (see WARNINGS; Cardiovascular Thrombotic Events, Gastrointestinal Bleeding, Ulceration, and Perforation, Hypertension, Renal Toxicity and Hyperkalemia).

Manage patients with symptomatic and supportive care following an NSAID overdosage. There are no specific antidotes. Hemodialysis does not decrease the plasma concentration of naproxen because of the high degree of its protein binding. Consider emesis and/or activated charcoal (60 to 100 g in adults, 1 to 2 g/kg of body weight in pediatric patients) and/or osmotic cathartic in symptomatic patients seen within four hours of ingestion or in patients with a large overdosage (5 to 10 times the recommended dosage). Forced diuresis, alkalinization of urine, hemodialysis, or hemoperfusion may not be useful due to high protein binding.

For additional information about overdosage treatment contact a poison control center (1-800-222-1222).

DOSAGE AND ADMINISTRATION

Carefully consider the potential benefits and risks of NAPROXEN, EC-NAPROXEN, NAPROXEN SODIUM and NAPROXEN SODIUM DS and other treatment options before deciding to use NAPROXEN, EC-NAPROXEN, NAPROXEN SODIUM and NAPROXEN SODIUM DS. Use the lowest effective dose for the shortest duration consistent with individual patient treatment goals (see WARNINGS; Gastrointestinal Bleeding, Ulceration, and Perforation).

After observing the response to initial therapy with NAPROXEN, EC-NAPROXEN, NAPROXEN SODIUM or NAPROXEN SODIUM DS, the dose and frequency should be adjusted to suit an individual patient’s needs.

Different dose strengths and formulations (ie, tablets, suspension) of the drug are not necessarily bioequivalent. This difference should be taken into consideration when changing formulation.

Although NAPROXEN, EC-NAPROXEN, NAPROXEN SODIUM and NAPROXEN SODIUM DS all circulate in the plasma as naproxen, they have pharmacokinetic differences that may affect onset of action. Onset of pain relief can begin within 30 minutes in patients taking naproxen sodium and within 1 hour in patients taking naproxen. Because EC-NAPROXEN dissolves in the small intestine rather than in the stomach, the absorption of the drug is delayed compared to the other naproxen formulations (see CLINICAL PHARMACOLOGY).

The recommended strategy for initiating therapy is to choose a formulation and a starting dose likely to be effective for the patient and then adjust the dosage based on observation of benefit and/or adverse events. A lower dose should be considered in patients with renal or hepatic impairment or in elderly patients (see WARNINGS; Hepatotoxicity, and Renal Toxicity and Hyperkalemia, and PRECAUTIONS; Geriatric Use).

Geriatric Patients

Studies indicate that although total plasma concentration of naproxen is unchanged, the unbound plasma fraction of naproxen is increased in the elderly. Caution is advised when high doses are required and some adjustment of dosage may be required in elderly patients. As with other drugs used in the elderly, it is prudent to use the lowest effective dose.

Patients With Moderate to Severe Renal Impairment

Naproxen-containing products are not recommended for use in patients with moderate to severe and severe renal impairment (creatinine clearance <30 mL/min) (see WARNINGS: Renal Effects).

Rheumatoid Arthritis, Osteoarthritis and Ankylosing Spondylitis

NAPROXEN | 250 mg or 375 mg or 500 mg | twice daily twice daily twice daily
NAPROXEN SODIUM | 275 mg (naproxen 250 mg with 25 mg sodium) | twice daily
NAPROXEN SODIUM DS | 550 mg (naproxen 500 mg with 50 mg sodium) | twice daily
EC-NAPROXEN | 375 mg or 500 mg | twice daily twice daily

To maintain the integrity of the enteric coating, the EC-NAPROXEN tablet should not be broken, crushed or chewed during ingestion. NAPROXEN Suspension should be shaken gently before use.

During long-term administration, the dose of naproxen may be adjusted up or down depending on the clinical response of the patient. A lower daily dose may suffice for long-term administration. The morning and evening doses do not have to be equal in size and the administration of the drug more frequently than twice daily is not necessary.

In patients who tolerate lower doses well, the dose may be increased to naproxen 1500 mg/day for limited periods of up to 6 months when a higher level of anti-inflammatory/analgesic activity is required. When treating such patients with naproxen 1500 mg/day, the physician should observe sufficient increased clinical benefits to offset the potential increased risk. The morning and evening doses do not have to be equal in size and administration of the drug more frequently than twice daily does not generally make a difference in response (see CLINICAL PHARMACOLOGY).

Juvenile Arthritis

Naproxen Tablets may not allow for the flexible dose titration needed in pediatric patients with juvenile arthritis. A liquid formulation may be more appropriate.

In pediatric patients, doses of 5 mg/kg/day produced plasma levels of naproxen similar to those seen in adults taking 500 mg of naproxen (see CLINICAL PHARMACOLOGY).

The recommended total daily dose of naproxen is approximately 10 mg/kg given in 2 divided doses. One-half of the 250 mg tablet will be needed for dosing lower-weight children. Dosing with Naproxen Tablets is not appropriate for children weighing less than 25 kilograms.

The recommended total daily dose of naproxen is approximately 10 mg/kg given in 2 divided doses (i.e., 5 mg/kg given twice a day). A measuring cup marked in 1/2 teaspoon and 2.5 milliliter increments is provided with the naproxen suspension. The following table may be used as a guide for dosing of naproxen suspension:

Patient’s Weight Dose Administered as

13 kg (29 lb) 62.5 mg bid 2.5 mL (1/2 tsp) twice daily

25 kg (55 lb) 125 mg bid 5.0 mL (1 tsp) twice daily

38 kg (84 lb) 187.5 mg bid 7.5 mL (1 1/2 tsp) twice daily

Management of Pain, Primary Dysmenorrhea, and Acute Tendonitis and Bursitis

The recommended starting dose is 550 mg of naproxen sodium as ANAPROX/ANAPROX DS followed by 550 mg every 12 hours or 275 mg every 6 to 8 hours as required. The initial total daily dose should not exceed 1375 mg of naproxen sodium. Thereafter, the total daily dose should not exceed 1100 mg of naproxen sodium. Because the sodium salt of naproxen is more rapidly absorbed, ANAPROX/ANAPROX DS is recommended for the management of acute painful conditions when prompt onset of pain relief is desired. NAPROXEN may also be used but EC-NAPROXEN is not recommended for initial treatment of acute pain because absorption of naproxen is delayed compared to other naproxen-containing products (see CLINICAL PHARMACOLOGY, INDICATIONS AND USAGE).

Acute Gout

The recommended starting dose is 750 mg of NAPROXEN followed by 250 mg every 8 hours until the attack has subsided. ANAPROX may also be used at a starting dose of 825 mg followed by 275 mg every 8 hours. EC-NAPROXEN is not recommended because of the delay in absorption (see CLINICAL PHARMACOLOGY).

HOW SUPPLIED

NAPROXEN Tablets: 250 mg: round, yellow, biconvex, engraved with NPR LE 250 on one side and scored on the other. Packaged in light-resistant bottles of 500.

500’s (bottle): NDC 42494-403-05.

375 mg: pink, biconvex oval, engraved with NPR LE 375 on one side. Packaged in light-resistant bottles of 500.

500’s (bottle): NDC 42494-404-05.

500 mg: yellow, capsule-shaped, engraved with NPR LE 500 on one side and scored on the other. Packaged in light-resistant bottles of 100 and 1000.

100’s (bottle): NDC 42494-405-01.

1000’s (bottle): NDC 42494-406-10.

Store at 15° to 30°C (59° to 86°F) in well-closed containers; dispense in light-resistant containers.

EC-NAPROXEN Delayed-Release Tablets: 375 mg: white, oval biconvex coated tablets imprinted with NPR EC 375 on one side. Packaged in light-resistant bottles of 100.

100’s (bottle): NDC 42494-407-01.

500 mg: white, oblong coated tablets imprinted with NPR EC 500 on one side. Packaged in light-resistant bottles of 100.

100’s (bottle): NDC 42494-408-01.

Store at 15° to 30°C (59° to 86°F) in well-closed containers; dispense in light-resistant containers.

NAPROXEN SODIUM Tablets:Naproxen sodium 275 mg: light blue, oval-shaped, engraved with NPS-275 on one side. Packaged in bottles of 100.

100’s (bottle): NDC 42494-402-01.

Store at 15° to 30°C (59° to 86°F) in well-closed containers.

NAPROXEN SODIUM DS Tablets:Naproxen sodium 550 mg: dark blue, oblong-shaped, engraved with NPS 550 on one side and scored on both sides. Packaged in bottles of 100 and 500.

100’s (bottle): NDC 42494-400-01.

500’s (bottle): NDC 42494-400-05.

Store at 15° to 30°C (59° to 86°F) in well-closed containers.

Manufactured for:
Cameron Pharmaceuticals, LLC
1009 Twilight Trail, Suite 107
Frankfort, Kentucky 40601

Medication Guide for Nonsteroidal Anti-inflammatory Drugs (NSAIDs)

What is the most important information I should know about medicines called Nonsteroidal Anti-inflammatory Drugs (NSAIDs)?

NSAIDs can cause serious side effects, including:

- Increased risk of a heart attack or stroke that can lead to death. This risk may happen early in treatment and may increase:
  - with increasing doses of NSAIDs
  - with longer use of NSAIDs

Do not take NSAIDs right before or after a heart surgery called a "coronary artery bypass graft (CABG)."

Avoid taking NSAIDs after a recent heart attack, unless your healthcare provider tells you to. You may have an increased risk of another heart attack if you take NSAIDs after a recent heart attack.

- Increased risk of bleeding, ulcers, and tears (perforation) of the esophagus (tube leading from the mouth to the stomach), stomach and intestines:
  - anytime during use
  - without warning symptoms
  - that may cause death

The risk of getting an ulcer or bleeding increases with:

- past history of stomach ulcers, or stomach or intestinal bleeding with use of NSAIDs
- taking medicines called "corticosteroids", "anticoagulants", "SSRIs", or "SNRIs"
- increasing doses of NSAIDs
- longer use of NSAIDs
- smoking
- drinking alcohol
- older age
- poor health
- advanced liver disease
- bleeding problems

NSAIDs should only be used:

- exactly as prescribed
- at the lowest dose possible for your treatment
- for the shortest time needed

What are NSAIDs?
NSAIDs are used to treat pain and redness, swelling, and heat (inflammation) from medical conditions such as different types of arthritis, menstrual cramps, and other types of short-term pain.

Who should not take NSAIDs?
Do not take NSAIDs:

- if you have had an asthma attack, hives, or other allergic reaction with aspirin or any other NSAIDs.
- right before or after heart bypass surgery.

Before taking NSAIDs, tell your healthcare provider about all of your medical conditions, including if you:

- have liver or kidney problems
- have high blood pressure
- have asthma
- are pregnant or plan to become pregnant. Talk to your healthcare provider if you are considering taking NSAIDs during pregnancy. You should not take NSAIDs after 29 weeks of pregnancy
- are breastfeeding or plan to breast feed.

Tell your healthcare provider about all of the medicines you take, including prescription or over-the-counter medicines, vitamins or herbal supplements. NSAIDs and some other medicines can interact with each other and cause serious side effects. Do not start taking any new medicine without talking to your healthcare provider first.

What are the possible side effects of NSAIDs?

NSAIDs can cause serious side effects, including:

See "What is the most important information I should know about medicines called Nonsteroidal Anti-inflammatory Drugs (NSAIDs)?

- new or worse high blood pressure
- heart failure
- liver problems including liver failure
- kidney problems including kidney failure
- low red blood cells (anemia)
- life-threatening skin reactions
- life-threatening allergic reactions
- Other side effects of NSAIDs include: stomach pain, constipation, diarrhea, gas, heartburn, nausea, vomiting, and dizziness.

Get emergency help right away if you get any of the following symptoms:

- shortness of breath or trouble breathing
- chest pain
- weakness in one part or side of your body
- slurred speech
- swelling of the face or throat

Stop taking your NSAID and call your healthcare provider right away if you get any of the following symptoms:

- nausea
- more tired or weaker than usual
- diarrhea
- itching
- your skin or eyes look yellow
- indigestion or stomach pain
- flu-like symptoms
- vomit blood
- there is blood in your bowel movement or it is black and sticky like tar
- unusual weight gain
- skin rash or blisters with fever
- swelling of the arms, legs, hands and feet

If you take too much of your NSAID, call your healthcare provider or get medical help right away.

These are not all the possible side effects of NSAIDs. For more information, ask your healthcare provider or pharmacist about NSAIDs.

Call your doctor for medical advice about side effects. You may report side effects to FDA at 1-800-FDA-1088.

Other information about NSAIDs

- Aspirin is an NSAID but it does not increase the chance of a heart attack. Aspirin can cause bleeding in the brain, stomach, and intestines. Aspirin can also cause ulcers in the stomach and intestines.
- Some NSAIDs are sold in lower doses without a prescription (over-the-counter). Talk to your healthcare provider before using over-the-counter NSAIDs for more than 10 days.

General information about the safe and effective use of NSAIDs

Medicines are sometimes prescribed for purposes other than those listed in a Medication Guide. Do not use NSAIDs for a condition for which it was not prescribed. Do not give NSAIDs to other people, even if they have the same symptoms that you have. It may harm them.

If you would like more information about NSAIDs, talk with your healthcare provider. You can ask your pharmacist or healthcare provider for information about NSAIDs that is written for health professionals.

Manufactured for:
Cameron Pharmaceuticals, LLC

1009 Twilight Trail, Suite 107
Frankfort, Kentucky 40601

This Medication Guide has been approved by the U.S. Food and Drug Administration.
Revised: May 2016

All registered trademarks in this document are the property of their respective owners.

Revised: July 2016

PRINCIPAL DISPLAY PANEL

NDC 42494-403-05
Naproxen Tablets
250 mg
500 Tablets
Rx Only

PRINCIPAL DISPLAY PANEL

NDC 42494-404-05
Naproxen Tablets
375 mg
500 Tablets
Rx Only

PRINCIPAL DISPLAY PANEL

NDC 42494-405-01
Naproxen Tablets
500 mg
100 Tablets
Rx Only

PRINCIPAL DISPLAY PANEL

NDC 42494-407-01
EC- Naproxen Delayed- Release Tablets
375 mg
100 Tablets
Rx Only

PRINCIPAL DISPLAY PANEL

NDC 42494-408-01
EC-Naproxen Delayed- Release Tablets
500 mg
100 Tablets
Rx Only

PRINCIPAL DISPLAY PANEL

NDC 42494-402-05
Naproxen Sodium Tablets
275 mg
100 Tablets
Rx Only

PRINCIPAL DISPLAY PANEL

NDC 42494-400-01
Naproxen Sodium DS Tablets
550 mg
100 Tablets
Rx Only